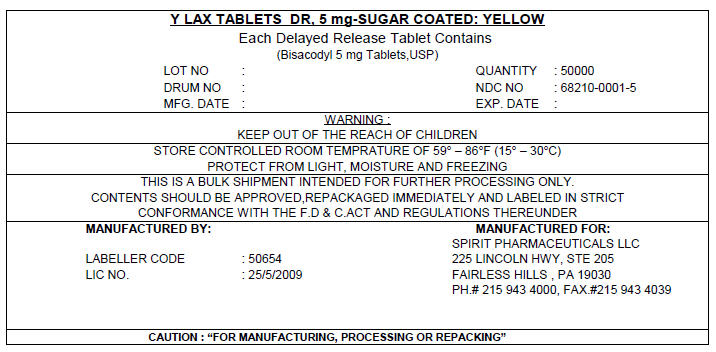 DRUG LABEL: Y LAX DR
NDC: 68210-0001 | Form: TABLET, SUGAR COATED
Manufacturer: SPIRIT PHARMACEUTICALS,LLC
Category: otc | Type: HUMAN OTC DRUG LABEL
Date: 20100421

ACTIVE INGREDIENTS: BISACODYL 5 mg/1 1
INACTIVE INGREDIENTS: LACTOSE; STARCH, CORN; POVIDONE K30; TALC; MAGNESIUM STEARATE; POLYETHYLENE GLYCOL; SUCROSE; ACACIA; METHYLPARABEN; FD&C YELLOW NO. 6; ALUMINUM OXIDE

Y LAX TABLETS DR, 5 mg-SUGAR COATED: YELLOW

Drug Facts

Active ingredients (in each tablet)

Bisacodyl 5 mg

Purpose

Stimulant laxative

Uses

- for relief of occasional constipation(irregularity)
- this product generally produces bowel movement in 6 to 12 hours

Warnings

Do not use if you cannot swallow without chewing

Ask a doctor before use if you have

- Stomach pain
- nausea
- vomiting
- noticed a sudden change in bowel habits that persists over a period of 2 weeks

When using this product

- do not chew or crush tablets
- do not take this product within 1 hour after taking an antacid or milk
- it may cause stomach discomfort,faintness, and cramps

Stop use and ask doctor if

- you need to use more than 1 week
- rectal bleeding or failure to have a bowel movement occur after use of a laxative.These may be signs of a serious condition

PREGNANCY OR BREAST FEEDING

If pregana or breast-feeding, ask a health professional before use

Keep out of reach of children.In case of overdose,get medical help or contact a poison control center right away.

Direction

take with a glass of water

- Do not take more than three tablets daily

adults and children 12 years of age and older | - take 1 to 3 tablets in a single dose once daily
children 6 to under 12 years of age | - take 1 tablet once daily
children under 6 years of age | - ask a doctor

Other information

- store between 20° to 25°C (68° to 77° F)
- protection from excessive humidity

Inactive ingredients

lactose,cornstarch,povidone (K-30),sodium startch glycolate,talc,magnesium stearate,methacrylic acid copolymer,polethylene glaycol,sodium hydroxide pellets, sucrose,acacia,gelatin,methylparaben, propylparaben, calcium sulphate dihydrate,titanium dioxide,D&C yellow #6 lake, FD & C yellow #10; pharmaceuticals glaze

PRINCIPAL DISPLAY PANEL - 5 mg Shipping Label

Y LAX TABLETS DR, 5 mg-SUGAR COATED: YELLOW

Each Delayed Release Tablet Contains

(Bisacodyl 5 mg Tablets,USP)

LOT NO :
DRUM NO :
MFG. DATE :

QUANTITY : 50000
NDC NO : 68210-0001-5
EXP. DATE :

WARNING :
KEEP OUT OF THE REACH OF CHILDREN

STORE CONTROLLED ROOM TEMPRATURE OF 59° – 86°F (15° – 30°C)
PROTECT FROM LIGHT, MOISTURE AND FREEZING

THIS IS A BULK SHIPMENT INTENDED FOR FURTHER PROCESSING ONLY.
CONTENTS SHOULD BE APPROVED,REPACKAGED IMMEDIATELY AND LABELED IN STRICT
CONFORMANCE WITH THE F.D & C.ACT AND REGULATIONS THEREUNDER

MANUFACTURED BY:

LABELLER CODE : 50654
LIC NO. : 25/5/2009

MANUFACTURED FOR:
SPIRIT PHARMACEUTICALS LLC
225 LINCOLN HWY, STE 205
FAIRLESS HILLS , PA 19030
PH.# 215 943 4000, FAX.#215 943 4039

CAUTION : "FOR MANUFACTURING, PROCESSING OR REPACKING"